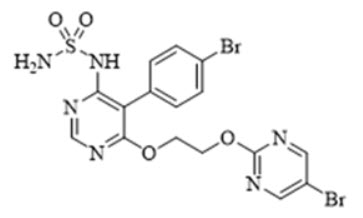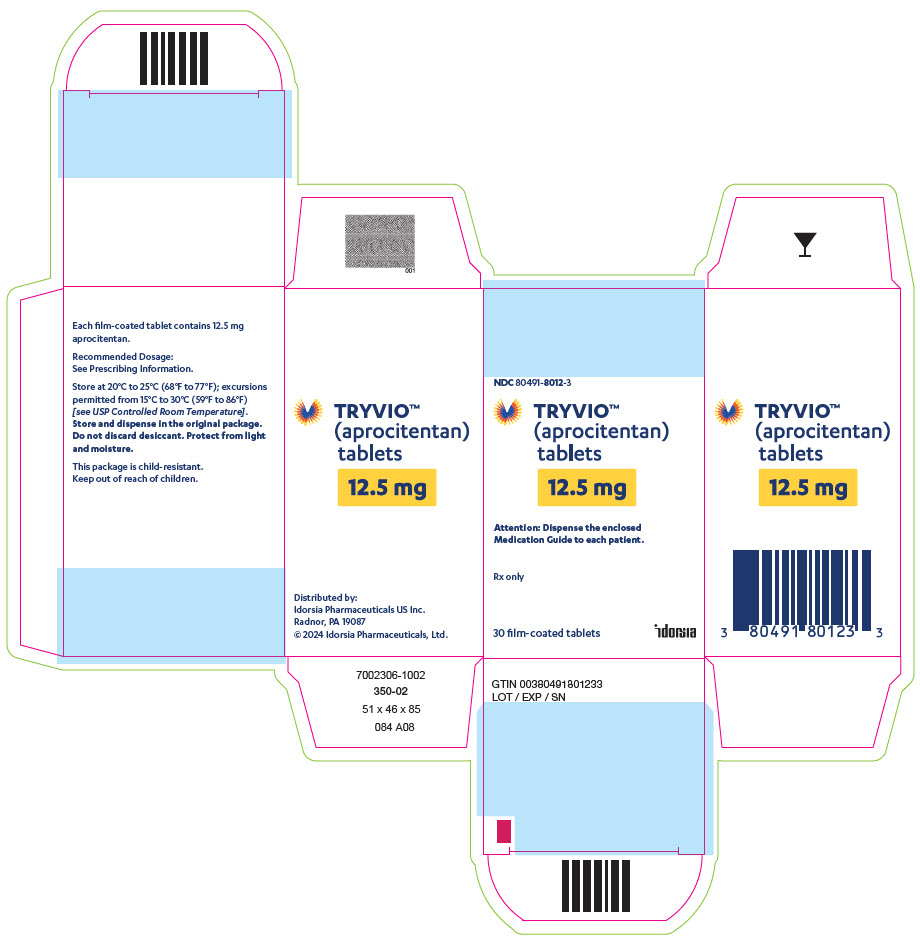 DRUG LABEL: TRYVIO
NDC: 80491-8012 | Form: TABLET, FILM COATED
Manufacturer: Idorsia Pharmaceuticals Ltd
Category: prescription | Type: HUMAN PRESCRIPTION DRUG LABEL
Date: 20260205

ACTIVE INGREDIENTS: APROCITENTAN 12.5 mg/1 1
INACTIVE INGREDIENTS: CROSCARMELLOSE SODIUM; HYDROXYPROPYL CELLULOSE, UNSPECIFIED; LACTOSE MONOHYDRATE; MAGNESIUM STEARATE; MICROCRYSTALLINE CELLULOSE; FERROSOFERRIC OXIDE; FERRIC OXIDE RED; FERRIC OXIDE YELLOW; POLYVINYL ALCOHOL, UNSPECIFIED; HYDRATED SILICA; TALC; TITANIUM DIOXIDE; TRIETHYL CITRATE

HIGHLIGHTS OF PRESCRIBING INFORMATION

These highlights do not include all the information needed to use TRYVIO safely and effectively. See full prescribing information for TRYVIO.
TRYVIO™ (aprocitentan) tablets, for oral use
Initial U.S. Approval: 2024

WARNING: EMBRYO-FETAL TOXICITY

See full prescribing information for complete boxed warning.

- Based on animal data TRYVIO may cause fetal harm if used by pregnant patients and is contraindicated in pregnancy. (4.1, 5.1, 8.1)
- For patients who can become pregnant, exclude pregnancy prior to initiation of treatment with TRYVIO. (2.2, 5.1, 8.3)
- Use effective contraception prior to initiation of treatment, during treatment, and for one month after stopping TRYVIO. (2.2, 4.1, 5.1, 8.3)
- When pregnancy is detected, discontinue TRYVIO as soon as possible (5.1)

RECENT MAJOR CHANGES

Boxed Warning | 4/2025
Contraindications (4.1) | 4/2025
Warnings and Precautions (5.1) | 4/2025

1 INDICATIONS AND USAGE

TRYVIO is an endothelin receptor antagonist indicated for the treatment of hypertension in combination with other antihypertensive drugs, to lower blood pressure in adult patients who are not adequately controlled on other drugs. Lowering blood pressure reduces the risk of fatal and non-fatal cardiovascular events, primarily strokes and myocardial infarctions. (1)

2 DOSAGE AND ADMINISTRATION

- The recommended dosage of TRYVIO is 12.5 mg orally once daily, with or without food. (2.1)

3 DOSAGE FORMS AND STRENGTHS

Tablets: 12.5 mg (3)

4 CONTRAINDICATIONS

- Pregnancy (4.1)
- Hypersensitivity (4.2)

5 WARNINGS AND PRECAUTIONS

- ERAs cause hepatotoxicity and liver failure. Measure serum aminotransferase levels and total bilirubin prior to initiation of treatment and repeat periodically during treatment and as clinically indicated. (5.2)
- Fluid retention may require intervention (5.3)
- Decreases in hemoglobin (5.4)
- Decreased sperm counts (5.5)

6 ADVERSE REACTIONS

Most common adverse reactions (more frequent than placebo and ≥ 2% in TRYVIO-treated patients) are edema/fluid retention and anemia. (6.1)

To report SUSPECTED ADVERSE REACTIONS, contact Idorsia Pharmaceuticals Ltd at 1-833-400-9611 or FDA at 1-800-FDA-1088 or www.fda.gov/medwatch.

8 USE IN SPECIFIC POPULATIONS

- Lactation: Advise not to breastfeed. (8.2)

FULL PRESCRIBING INFORMATION

WARNING: EMBRYO-FETAL TOXICITY

- TRYVIO is contraindicated for use during pregnancy because it may cause fetal harm if used by pregnant patients. Therefore in patients who can become pregnant, exclude pregnancy prior to initiation of TRYVIO.
- Advise use of effective contraception before the start of TRYVIO, during treatment and for one month after stopping treatment.
- When pregnancy is detected, discontinue TRYVIO as soon as possible [see Dosage and Administration (2.2), Contraindications (4.1), Warnings and Precautions (5.1), Use in Specific Populations (8.1)].

1 INDICATIONS AND USAGE

TRYVIO, in combination with other antihypertensive drugs, is indicated for the treatment of hypertension, to lower blood pressure (BP) in adult patients who are not adequately controlled on other drugs. Lowering BP reduces the risk of fatal and non-fatal cardiovascular events, primarily strokes and myocardial infarctions. These benefits have been seen in controlled trials of antihypertensive drugs from a wide variety of pharmacologic classes. There are no controlled trials demonstrating reduction of risk of these events with TRYVIO.

Control of high BP should be part of comprehensive cardiovascular risk management, including, as appropriate, lipid control, diabetes management, antithrombotic therapy, smoking cessation, exercise, and limited sodium intake. Many patients will require more than one drug to achieve BP goals. For specific advice on goals and management, see published guidelines, such as those of the National High Blood Pressure Education Program's Joint National Committee on Prevention, Detection, Evaluation, and Treatment of High Blood Pressure (JNC).

Numerous antihypertensive drugs, from a variety of pharmacologic classes and with different mechanisms of action, have been shown in randomized controlled trials to reduce cardiovascular morbidity and mortality, and it can be concluded that it is BP reduction, and not some other pharmacologic property of the drugs, that is largely responsible for those benefits. The largest and most consistent cardiovascular outcome benefit has been a reduction in the risk of stroke, but reductions in myocardial infarction and cardiovascular mortality also have been seen regularly.

Elevated systolic or diastolic pressure causes increased cardiovascular risk, and the absolute risk increase per mmHg is greater at higher BPs, so that even modest reductions of severe hypertension can provide substantial benefit. Relative risk reduction from BP reduction is similar across populations with varying absolute risk, so the absolute benefit is greater in patients who are at higher risk independent of their hypertension (for example, patients with diabetes or hyperlipidemia), and such patients would be expected to benefit from more aggressive treatment to a lower BP goal.

2 DOSAGE AND ADMINISTRATION

2.1 Recommended Dosage

The recommended dosage of TRYVIO is 12.5 mg orally once daily.

Swallow tablets whole. TRYVIO may be taken with or without food.

If a dose is missed, skip the missed dose and take the next dose at the regular time. Do not take two doses on the same day.

2.2 Pregnancy Testing in Females of Reproductive Potential

Exclude pregnancy before initiating treatment with TRYVIO in females of reproductive potential [see Boxed Warning, Contraindications (4.1), Warnings and Precautions (5.1), Use in Specific Populations (8.3)].

3 DOSAGE FORMS AND STRENGTHS

TRYVIO (aprocitentan) tablets are available as:

- 12.5 mg: yellow to orange round, film-coated tablet, debossed with "AN" on one side and plain on the other side.

4 CONTRAINDICATIONS

4.1 Pregnancy

Use of TRYVIO is contraindicated in patients who are pregnant [see Dosage and Administration (2.2), Warnings and Precautions (5.1) and Use in Specific Populations (8.1)].

4.2 Hypersensitivity

TRYVIO is contraindicated in patients who are hypersensitive to aprocitentan or any of its excipients [see Adverse Reactions (6.1)].

5 WARNINGS AND PRECAUTIONS

5.1 Embryo-Fetal Toxicity

Based on data from animal reproduction studies with endothelin receptor antagonists (ERAs), TRYVIO may cause fetal harm when administered during pregnancy and is contraindicated for use in patients who are pregnant. The available human data for endothelin receptor antagonists do not establish the presence or absence of fetal harm related to the use of TRYVIO. Counsel patients who can become pregnant about the potential risk to a fetus. Obtain a pregnancy test prior to initiation of treatment with TRYVIO. Advise patients who can become pregnant to use effective contraception prior to initiation of treatment with TRYVIO, during treatment, and for one month after the final dose of TRYVIO. When pregnancy is detected, discontinue TRYVIO as soon as possible [see Dosage and Administration (2.2), Contraindications (4.1), Use in Specific Populations (8.1, 8.3)].

5.2 Hepatotoxicity

Elevations of aminotransferases and hepatotoxicity are known effects of ERAs, including TRYVIO. Elevations in alanine transaminase (ALT) or aspartate aminotransferase (AST) of greater than 5-fold upper limit of normal (ULN) were observed rarely in patients treated with aprocitentan in the clinical trial, including cases with positive rechallenge. There were no reports of patients with ALT and/or AST >3 × ULN and total bilirubin >2 × ULN or cases of liver failure observed in TRYVIO-treated patients in the clinical trials. To reduce the risk of potential serious hepatotoxicity, measure serum aminotransferase levels and total bilirubin prior to initiation of treatment and repeat during treatment periodically and as clinically indicated.

Do not initiate TRYVIO in patients with elevated aminotransferases (>3 × ULN) or moderate to severe hepatic impairment.

Advise patients with symptoms suggesting hepatotoxicity (nausea, vomiting, right upper quadrant pain, fatigue, anorexia, scleral icterus, jaundice, dark urine, fever, or itching) to immediately stop treatment with TRYVIO and seek medical attention.

If sustained, unexplained, clinically relevant aminotransferase elevations occur, or if elevations are accompanied by an increase in bilirubin >2 × ULN, or if clinical symptoms of hepatotoxicity occur, discontinue TRYVIO.

5.3 Fluid Retention

Fluid retention and peripheral edema are known effects of ERAs, including TRYVIO [see Adverse Reactions (6.1)]. Edema/fluid retention was reported in 9% of TRYVIO-treated patients compared with 18% of patients receiving aprocitentan 25 mg (twice the recommended dose) and 2% on placebo in the clinical trial, requiring additional diuretic use in some patients. Older age and chronic kidney disease are risk factors for edema/fluid retention with TRYVIO. TRYVIO has not been studied in patients with heart failure New York Heart Association stage III–IV, unstable cardiac function, or with NTproBNP ≥500 pg/mL. TRYVIO is not recommended in these patients.

Monitor for signs and symptoms of fluid retention, weight gain, and worsening heart failure. If clinically significant fluid retention develops, treat appropriately, and consider discontinuation of TRYVIO.

5.4 Hemoglobin Decrease

Decreases in hemoglobin concentration and hematocrit have occurred following administration of other ERAs and were observed in the clinical trial with TRYVIO. Hemoglobin decreases usually presented early, stabilized thereafter, and were reversible after discontinuation. A decrease in hemoglobin of >2 g/dL from baseline was observed in 7% of patients compared to 1% of placebo patients. A decrease to below 10.0 g/dL was observed in 3% of TRYVIO-treated patients compared to 0 patients taking placebo. Initiation of TRYVIO is not recommended in patients with severe anemia. Measure hemoglobin prior to initiation of treatment and periodically during treatment as clinically indicated [see Adverse Reactions (6.1)].

5.5 Decreased Sperm Counts

TRYVIO, like other ERAs, may have an adverse effect on spermatogenesis. Counsel men about potential effects on fertility [see Use in Specific Populations (8.3) and Nonclinical Toxicology (13.1)].

6 ADVERSE REACTIONS

Clinically significant adverse reactions that appear in other sections of the labeling include:

- Embryo-fetal toxicity [see Warnings and Precautions (5.1)]
- Hepatotoxicity [see Warnings and Precautions (5.2)]
- Fluid retention [see Warnings and Precautions (5.3)]
- Hemoglobin decrease [see Warnings and Precautions (5.4)]
- Decreased sperm counts [see Warnings and Precautions (5.5)]

6.1 Clinical Trials Experience

Because clinical trials are conducted under widely varying conditions, adverse reaction rates observed in the clinical trials of a drug cannot be directly compared to rates in the clinical trials of another drug and may not reflect the rates observed in practice.

The safety of TRYVIO was evaluated in a placebo-controlled phase 3 clinical study (PRECISION, NCT03541174) in adults with uncontrolled BP (systolic blood pressure [SBP] ≥140 mmHg) despite the use of at least three antihypertensive medications.

In this study, 724 patients received any dose of aprocitentan, with 633 patients treated for at least 26 weeks, 192 patients for at least 47 weeks, and 99 patients for at least 48 weeks.

The most frequently reported adverse reactions to TRYVIO during the 4-week double-blind placebo-controlled treatment period (part 1) of the PRECISION study are presented in Table 1.

Table 1 Adverse reactions reported with a frequency of ≥2% in TRYVIO-treated patients and greater (≥1%) than in placebo-treated patients during the initial 4-week double-blind placebo-controlled treatment (part 1)
Adverse Reaction | 12.5 mg N = 243 % | Placebo N = 242 %
Edema/fluid retention | 9.1 | 2.1
Anemia | 3.7 | 0

Hypersensitivity Reactions

During the initial 4-week double-blind placebo-controlled treatment period (part 1), 0.8% of patients experienced an adverse reaction of hypersensitivity (i.e., rash, erythema, allergic edema) on TRYVIO compared to no reports in patients treated with placebo. One patient experienced allergic dermatitis requiring hospitalization while receiving aprocitentan 25 mg.

Laboratory Tests

Initiation of TRYVIO may cause an initial small decrease in estimated glomerular filtration rate (eGFR) that occurs within the first 6 weeks of starting therapy and then stabilizes.

In the initial 4-week double-blind treatment period, TRYVIO 12.5 mg caused a mean decrease of about 0.8 g/dL in hemoglobin compared to no change in the placebo patients.

8 USE IN SPECIFIC POPULATIONS

8.1 Pregnancy

Risk Summary

Based on animal reproduction studies with other ERAs, TRYVIO can cause embryo-fetal toxicity, including birth defects and fetal death when administered to a pregnant patient and is contraindicated during pregnancy [see Contraindications (4.1)]. Available data from post-marketing reports and published literature over decades of use with endothelin receptor antagonists in the same class as TRYVIO have not identified an increased risk of fetal harm; however, these data are limited. Methodological limitations of these post-marketing reports and published literature include lack of a control group; limited information regarding dose, duration, and timing of drug exposure; and missing data. These limitations preclude establishing a reliable estimate of the risk of adverse fetal and neonatal outcomes with maternal endothelin receptor antagonist use. Administration of macitentan, where approximately ≥50% of total exposure was to aprocitentan, was teratogenic in rats and rabbits at all doses tested (see Data). Available data from reports of pregnancy in clinical trials with TRYVIO are insufficient to rule out a drug-associated risk of major birth defects, miscarriage or other adverse maternal or fetal outcomes. Advise pregnant patients of the potential risk to a fetus.

The background risk of major birth defects and miscarriage for the indicated population is unknown. All pregnancies have a background risk of birth defect, loss, or other adverse outcomes. In the U.S. general population, the estimated background risk of major birth defects and miscarriage in clinically recognized pregnancies is 2% to 4% and 15% to 20%, respectively.

Data

Animal Data

In embryo-fetal development toxicity studies in pregnant rats and rabbits given macitentan (for which aprocitentan is a major metabolite) during the period of major organogenesis, cardiovascular and mandibular arch fusion malformations were observed at all doses studied. The lowest doses in rats and rabbits produced aprocitentan exposures that were equivalent to and 15-fold, respectively, the clinical exposures at the maximum recommended human dose (MRHD) based on area under the curve (AUC).

In pre- and post-natal development studies, female rats given macitentan (for which aprocitentan is a major metabolite) from late pregnancy through lactation showed reduced pup survival and impairment of the male fertility of the offspring at all doses. The lowest dose produced aprocitentan exposures approximately 2-fold the clinical exposures at the MRHD based on AUC.

8.2 Lactation

Risk Summary

There are no data on the presence of aprocitentan in human milk, the effects on the breastfed infant, or the effect on milk production. In rats, aprocitentan was excreted into milk during lactation (see Data). When a drug is present in animal milk, it is likely that the drug will be present in human milk. Because of the potential for serious adverse reactions in breastfed infants, advise women not to breastfeed during treatment with TRYVIO.

Data

A single ^14C-radiolabeled macitentan dose of 3 mg/kg was given orally to lactating Wistar rats. Aprocitentan was consistently observed in milk samples across all collection times after oral administration.

8.3 Females and Males of Reproductive Potential

Based on data from animal reproductive toxicity studies with other ERAs, TRYVIO can cause fetal harm, including birth defects and fetal death, when administered to a pregnant patient and is contraindicated during pregnancy [see Contraindications (4.1), Use in Specific Populations (8.1)].

Pregnancy Testing

Verify that patients who can become pregnant, are not pregnant prior to initiating TRYVIO. The patient should contact their physician immediately if onset of menses is delayed or pregnancy is suspected. If the pregnancy test is positive, the physician and patient should discuss the risks to the patient, the pregnancy, and the fetus [see Warnings and Precautions (5.1), Dosage and Administration (2.2), Contraindications (4.1)].

Contraception

Patients using TRYVIO who can become pregnant should use effective contraception prior to initiation of treatment, during treatment, and for one month after discontinuation of treatment with TRYVIO to prevent pregnancy [see Warnings and Precautions (5.1)].

Infertility

Other ERAs have shown an adverse effect on spermatogenesis in humans and/or animals. TRYVIO, like other ERAs, may impair fertility in males of reproductive potential. It is not known whether effects on fertility would be reversible [see Warnings and Precautions (5.5), Nonclinical Toxicology (13.1)].

8.4 Pediatric Use

The safety and efficacy of TRYVIO in pediatric patients have not been established.

8.5 Geriatric Use

Of the total number of subjects in the PRECISION study of TRYVIO, 321 (44%) were 65 years and older, while 72 (10%) were 75 years and older. Edema/fluid retention was more common in these patients than younger patients [see Warnings and Precautions (5.3)].

No dose adjustment is required in patients over the age of 65 years [see Clinical Pharmacology (12.3)].

8.6 Renal Impairment

TRYVIO is not recommended in patients with kidney failure (eGFR <15 mL/min) or on dialysis. The effect of kidney failure (eGFR <15 mL/min) or dialysis on aprocitentan pharmacokinetics is unknown [see Clinical Pharmacology (12.3)]. Patients with renal impairment are at increased risk of edema/fluid retention [see Warnings and Precautions (5.3)].

No dose adjustment is required in patients with mild to severe renal impairment (eGFR ≥15 mL/min).

8.7 Hepatic Impairment

TRYVIO is not recommended in patients with moderate and severe hepatic impairment (Child-Pugh class B and C) because these patients may be at increased risk for poor outcomes from hepatotoxicity.

No dose adjustment is required in patients with mild hepatic impairment (Child-Pugh class A) [see Clinical Pharmacology (12.3)].

10 OVERDOSAGE

TRYVIO has been administered as a single dose of up to 600 mg, and as multiple doses of up to 100 mg daily, to healthy subjects (48 and 8 times the recommended dose, respectively). Adverse events of headache, nasal congestion, nausea, and upper respiratory tract infection were observed. In the event of an overdose, standard supportive measures should be taken, as required. Dialysis is unlikely to be effective because aprocitentan is highly protein-bound. Consult a Certified Poison Control Center for the most up-to-date information on the management of overdosage (1-800-222-1222 or www.poison.org).

11 DESCRIPTION

TRYVIO (aprocitentan) is an endothelin receptor antagonist. The chemical name of aprocitentan is N-[5-(4-bromophenyl)-6- [2-[(5-bromo-2-pyrimidinyl)oxy]ethoxy]-4-pyrimidinyl]-sulfamide. It has a molecular formula of C16H14Br2N6O4S and a molecular weight of 546.2 g/mol.

The structural formula is:

Aprocitentan is a white to off-white powder that is insoluble in water.

TRYVIO is available as film-coated 12.5 mg strength tablets for oral administration. The inactive ingredients in TRYVIO are croscarmellose sodium, hydroxypropyl cellulose, lactose monohydrate, magnesium stearate, and microcrystalline cellulose.

The film coating contains the following inactive ingredients: hydroxypropyl cellulose, iron oxide black, iron oxide red, iron oxide yellow, polyvinyl alcohol, silica colloidal hydrated, talc, titanium dioxide, and triethyl citrate.

12 CLINICAL PHARMACOLOGY

12.1 Mechanism of Action

Aprocitentan is an ERA that inhibits the binding of endothelin (ET)-1 to ETA and ETB receptors.

ET-1, via its receptors (ETA and ETB), mediates a variety of deleterious effects such as vasoconstriction, fibrosis, cell proliferation, and inflammation. In hypertension, ET-1 can cause endothelial dysfunction, vascular hypertrophy and remodeling, sympathetic activation, and increased aldosterone synthesis.

12.2 Pharmacodynamics

Aprocitentan exposure-response relationships and the time course of pharmacodynamic response are not fully characterized.

Cardiac Electrophysiology

At eight times the recommended dose, clinically significant QTc interval prolongation was not observed.

12.3 Pharmacokinetics

The aprocitentan mean (%CV) Cmax is approximately 1.3 mcg/mL (19) following a single 25 mg dose (twice the recommended dose). The mean (%CV) aprocitentan AUC to the dosing interval (AUC0-tau) is approximately 23 mcg⸱h/mL (17) following a single 25 mg dose. Aprocitentan plasma concentrations increased in a dose-proportional manner following once-daily administration of 5, 25, and 100 mg (0.4 times the recommended dose to 8 times the recommended dose). Aprocitentan steady state is reached by Day 8 with approximately 3-fold accumulation following once daily administration. Aprocitentan is primarily unchanged in plasma following oral TRYVIO administration.

Absorption

The absolute oral bioavailability of aprocitentan is unknown. The time to reach Cmax is between 4 and 5 hours after administration of 25 mg aprocitentan (twice the recommended dose).

Effect of Food

No clinically significant differences in aprocitentan pharmacokinetics were observed following administration of a high-fat, high-calorie meal (approximately 150, 250, and 500–600 calories from protein, carbohydrate, and fat, respectively) in healthy subjects.

Distribution

The apparent volume of distribution of aprocitentan is approximately 20 L. Aprocitentan is >99% bound to plasma proteins, primarily albumin. Protein binding is not affected by renal or hepatic impairment. The aprocitentan blood-to-plasma ratio is 0.63.

Elimination

The aprocitentan effective half-life is approximately 41 hours, and the apparent clearance is approximately 0.3 L/h.

Metabolism

Aprocitentan is primarily metabolized by UGT1A1- and UGT2B7-mediated N-glucosidation and non-enzymatic hydrolysis.

Excretion

After a single dose of radiolabeled aprocitentan, approximately 52% of the dose was eliminated via urine (0.2% unchanged) and 25% via feces (6.8% unchanged).

Specific Populations

No clinically significant differences in the pharmacokinetics of aprocitentan were observed based on age (18–84 years), sex, race/ethnicity, body weight (44–196 kg), between patients and healthy subjects, mild to severe renal impairment (eGFR ≥15 mL/min), or mild to moderate hepatic impairment (Child-Pugh class A to B). The effect of kidney failure (eGFR <15 mL/min), dialysis, or severe hepatic impairment (Child-Pugh class C) on aprocitentan pharmacokinetics is unknown.

Drug Interaction Studies

Clinical Studies and Model-Informed Approaches

No clinically significant differences in the pharmacokinetics of the following drugs were observed when used concomitantly with aprocitentan: midazolam (CYP3A4 substrate), rosuvastatin (breast cancer resistance protein [BCRP] substrate) or oral contraceptive (ethinyl estradiol and levonorgestrel).

In Vitro Studies

UDP-glucuronosyltransferase (UGT) inducers: Concomitant administration of aprocitentan with UGT inducers may decrease aprocitentan exposure.

CYP450 enzymes: Aprocitentan inhibits CYP3A4 and all members of the CYP2C family, but did not inhibit CYP1A2, CYP2A6, CYP2B6, CYP2D6, and CYP2E1. Aprocitentan is an inducer of CYP3A4 but did not induce CYP1A2 or CYP2C9.

UGT enzymes: Aprocitentan is a substrate and inhibitor of UGT1A1 and UGT2B7.

Transporter systems: Aprocitentan is a substrate of P-glycoprotein (P-gp) and BCRP. However, inhibitors of these transporters are not anticipated to influence the PK of aprocitentan. Aprocitentan is an inhibitor of BCRP, bile salt export pump (BSEP), and sodium taurocholate co-transporting polypeptide (NTCP), but does not inhibit P-gp, organic cationic transporter (OCT)1, OCT2, human multi-drug and toxin compound extrusion (MATE)1, or MATE2K. Aprocitentan does not inhibit organic anion transporter (OAT)1, OAT3, OATP1B1, or OATP1B3 at therapeutic concentrations.

13 NONCLINICAL TOXICOLOGY

13.1 Carcinogenesis, Mutagenesis, Impairment of Fertility

Carcinogenesis

Two-year carcinogenicity studies with macitentan (for which aprocitentan is a major metabolite) did not identify any carcinogenic potential at doses up to 100 mg/kg/day and 250 mg/kg/day in mice and rats, which produced aprocitentan exposures approximately 30-fold and 11-fold, respectively, the clinical aprocitentan exposure at the MRHD based on AUC.

Mutagenesis

Aprocitentan did not induce mutagenicity or genotoxicity in a standard battery of in vitro and in vivo assays that included a bacterial reverse mutation assay, a chromosome aberration test in human lymphocytes, and an in vivo bone marrow micronucleus test in rats.

Impairment of Fertility

In a fertility study in male rats given aprocitentan for 15 weeks at doses up to 250 mg/kg/day, no effect on fertility or spermatogenesis was observed at 52-fold the clinical exposure at the MRHD based on AUC. In repeated dose toxicity studies, treatment with aprocitentan resulted in testicular tubular degeneration/atrophy in male rats and dogs at high doses of 250 mg/kg/day and 25 mg/kg/day, respectively, which represents approximately 41- and 52-fold the clinical exposure at the MRHD, based on AUC, respectively. The testicular toxicity was not evident in male rats and dogs at 50 mg/kg/day and 5 mg/kg/day, respectively, which represents approximately 14- and 10-fold the clinical exposure at the MRHD based on AUC.

In female rats given aprocitentan prior to mating, minimally increased pre-implantation loss was observed at doses ≥50 mg/kg/day, which represent ≥23-fold the clinical exposure at the MRHD based on AUC. No impact on fertility was observed at 10 mg/kg/day, which represents 5-fold the clinical exposure at the MRHD based on AUC.

14 CLINICAL STUDIES

The efficacy of TRYVIO (aprocitentan) was evaluated in a multipart, phase 3 multicenter study (PRECISION, NCT03541174) in adults with SBP ≥140 mmHg who were prescribed at least three antihypertensive medications. The trial included a placebo run-in period, which was followed by three parts as described below. Prior to the placebo run-in period, all patients were switched to standard background antihypertensive therapy consisting of an angiotensin receptor blocker, a calcium channel blocker, and a diuretic, which was continued throughout the study. Patients with concomitant use of beta-blockers continued this treatment throughout the study.

Following the 4-week placebo run-in period, 730 patients were randomized equally to aprocitentan at either 12.5 mg, 25 mg, or placebo once daily during the initial 4-week double-blind (DB) treatment period (part 1). At the end of 4 weeks, all patients entered the single-blind treatment period (part 2) where they received 25 mg aprocitentan once daily for 32 weeks. At the end of the 32 weeks, patients were re-randomized to receive either 25 mg aprocitentan or placebo, once daily, during a 12-week DB-withdrawal period (part 3).

The primary efficacy endpoint was the change in sitting SBP (SiSBP) from baseline to Week 4 during part 1, measured at trough by unattended automated office blood pressure (uAOBP).

The key secondary endpoint was the change in SiSBP measured at trough by uAOBP from Week 36 (i.e., prior to randomized withdrawal to 25 mg aprocitentan or placebo in part 3) to Week 40.

Patients had a mean age of 62 years (range 24 to 84 years) and 60% were male. Patients were White (83%), African American (11%) or Asian (5%). Approximately 10% were Hispanic. The mean body mass index (BMI) was 34 kg/m^2 (range 18 to 64 kg/m^2). At baseline, 19% of patients had an eGFR 30–59 mL/min/1.73 m^2 and 3% had an eGFR 15–29 mL/min/1.73 m^2. At baseline, 24% of patients had a urine albumin-to-creatinine ratio (UACR) of 30–300 mg/g and 13% had a UACR >300 mg/g. Approximately 54% of patients had a medical history of diabetes mellitus, 31% ischemic heart disease, and 20% congestive heart failure. At baseline, 63% of patients reported taking four or more antihypertensive medications.

BP reductions compared to placebo based on uAOBP measurements at trough are shown in Table 2. TRYVIO 12.5 mg was statistically superior to placebo in reducing SiSBP at Week 4 (part 1). The treatment effect was consistent for sitting diastolic BP (SiDBP) (Table 2).

Table 2 Reduction in sitting trough BP (mmHg) at Week 4 of DB treatment
 |  |  |  | Difference to placebo
Treatment group | N | Baseline [Observed baseline value.] Mean | LS Mean | LS Mean | p-value
SiSBP (primary endpoint) |  |  | LS Mean (97.5% CL) | LS Mean (97.5% CL)
12.5 mg | 243 | 153.2 | −15.4 (−17.5, −13.3) | −3.8 (−6.8, −0.8) | 0.0043 [Statistically significant at the 2.5% level as prespecified in the testing strategy.]
Placebo | 244 | 153.3 | −11.6 (−13.7, −9.5) | – | –
SiDBP |  |  | LS Mean (97.5% CL) | LS Mean (97.5% CL)
12.5 mg | 243 | 87.9 | −10.4 (−11.7, −9.1) | −4.0 (−5.8, −2.1) | −
Placebo | 244 | 87.1 | −6.4 (−7.8, −5.1) | – | –
BP = blood pressure; CL = confidence limits; DB = double-blind; LS Mean = least squares mean; SiDBP = sitting diastolic blood pressure; SiSBP = sitting systolic blood pressure.

The persistence of the BP-lowering effect of TRYVIO was demonstrated in part 3 of the trial, in which patients on aprocitentan were re-randomized to placebo or 25 mg aprocitentan following a period during which all patients were treated with 25 mg. In patients re-randomized to placebo, the mean SiSBP increased, whereas in patients re-randomized to 25 mg aprocitentan the mean effect on SiSBP was maintained and was statistically superior to placebo at Week 40. The treatment effect was consistent for SiDBP.

Most of the BP-lowering effect occurred within the first two weeks of treatment with TRYVIO.

TRYVIO is not approved for use at a 25 mg dose. The 25 mg dose has not demonstrated a meaningful improvement in blood pressure reduction as compared to the 12.5 mg dose and had an increased risk of edema/fluid retention [see Warnings and Precautions (5.3)].

TRYVIO's BP-lowering effect appeared consistent among subgroups defined by age, sex, race, BMI, baseline eGFR, baseline UACR, medical history of diabetes, and between BP measurement methodologies (uAOBP and ambulatory BP measurements).

16 HOW SUPPLIED/STORAGE AND HANDLING

16.1 How Supplied

TRYVIO tablets are available as:

- 12.5 mg: yellow to orange round, film-coated tablet, debossed with "AN" on one side and plain on the other side.
  1. NDC 80491-8012-8, each blister contains 10 tablets
  2. NDC 80491-8012-3, each bottle contains 30 tablets and has a child-resistant closure

16.2 Storage and Handling

Store at 20ºC to 25ºC (68ºF to 77ºF); excursions permitted from 15ºC to 30ºC (59ºF to 86ºF) [see USP Controlled Room Temperature]. Store in the original package. Dispense to patient in original container only. Replace cap securely each time after opening. Do not discard desiccant. Protect from light and moisture.

17 PATIENT COUNSELING INFORMATION

Advise the patient to read the FDA-approved patient labeling (Medication Guide).

Embryo-Fetal Toxicity

Counsel patients who can become pregnant to use effective methods of contraception before treatment with TRYVIO, during treatment with TRYVIO, and for one month after treatment discontinuation. Patients who can become pregnant should have a negative pregnancy test prior to initiation of TRYVIO, [see Warnings and Precautions (5.1) and Use in Specific Populations (8.1, 8.3)].

Patients should be instructed to contact their healthcare provider if they suspect they may be pregnant. Patients should seek additional contraceptive advice from a gynecologist or similar expert as needed.

Educate and counsel patients who can become pregnant on the use of emergency contraception in the event of unprotected sex or contraceptive failure.

Advise pre-pubertal females and/or their guardian(s) to report any changes in their reproductive status immediately to their prescriber.

Lactation

Advise females not to breastfeed during treatment with TRYVIO [see Use in Specific Populations (8.2)].

Hepatotoxicity

Educate patients on signs of hepatotoxicity. Advise patients that they should contact their healthcare provider if they have unexplained nausea, vomiting, right upper quadrant pain, fatigue, anorexia, jaundice, dark urine, fever, or itching.

Fluid Retention

Educate patients on signs of fluid retention. Advise patients that they should contact their healthcare provider if they have unusual weight increase or swelling of the ankles or legs.

Distributed by:
Idorsia Pharmaceuticals US Inc.
One Radnor Corporate Center, Suite 101
100 Matsonford Rd.
Radnor, PA 19087

IDRSTRPI09112025

Patent: www.idorsia.com/patents

MEDICATION GUIDE
TRYVIO™ (try-vee-oh)
(aprocitentan)
tablets, for oral use

Read this Medication Guide before you start taking TRYVIO and each time you get a refill. There may be new information. This Medication Guide does not take the place of talking to your healthcare provider about your medical condition or your treatment.

What is the most important information I should know about TRYVIO?
TRYVIO may cause serious side effects, including:
Serious birth defects.

- TRYVIO may cause serious birth defects if taken during pregnancy.
- Females who can become pregnant should not be pregnant when they start taking TRYVIO or become pregnant during treatment with TRYVIO or for 1 month after stopping treatment with TRYVIO.
- Females who can become pregnant should have a negative pregnancy test before starting treatment with TRYVIO.
  - Females who can become pregnant are females who:
    - have entered puberty, even if they have not started their menstrual period, and
    - have a uterus, and
    - have not gone through menopause. Menopause means that you have not had a menstrual period for at least 12 months for natural reasons, or that you have had your ovaries removed.
  - Females who cannot become pregnant are females who:
    - have not yet entered puberty, or
    - do not have a uterus, or
    - have gone through menopause. Menopause means that you have not had a menstrual period for at least 12 months for natural reasons, or that you have had your ovaries removed, or
    - are infertile for other medical reasons and this infertility is permanent and cannot be reversed.
- Females who can become pregnant should use effective birth control before starting treatment with TRYVIO, during treatment with TRYVIO, and for 1 month after stopping TRYVIO because the medicine may still be in your body.
  - Talk with your healthcare provider or gynecologist (a healthcare provider who specializes in female reproduction) to find out about options for effective birth control that you may use to prevent pregnancy during treatment with TRYVIO.
  - If you decide that you want to change the form of birth control that you use, talk with your healthcare provider or gynecologist to be sure that you choose another acceptable form of birth control.

- Do not have unprotected sex. Talk to your healthcare provider or pharmacist right away if you have unprotected sex or if you think your birth control has failed. Your healthcare provider may talk with you about using emergency birth control.
- Tell your healthcare provider right away if you miss a menstrual period or you think you might be pregnant.

See "What are the possible side effects of TRYVIO?" for more information about side effects.

What is TRYVIO?
TRYVIO is a prescription medicine used to treat high blood pressure (hypertension) in adults who are taking other high blood pressure medicines and whose blood pressure is not well controlled.
It is not known if TRYVIO is safe and effective in children.

Who should not take TRYVIO?
Do not take TRYVIO if you are:

- pregnant or currently trying to become pregnant. See "What is the most important information I should know about TRYVIO?".
- allergic to aprocitentan or any of the ingredients in TRYVIO. See the end of this Medication Guide for a complete list of ingredients in TRYVIO.

Before taking TRYVIO, tell your healthcare provider about all of your medical conditions, including if you:

- have liver problems
- have heart failure
- have anemia
- have kidney problems or get dialysis
- are pregnant or plan to become pregnant during treatment with TRYVIO. TRYVIO can cause serious birth defects. See "What is the most important information I should know about TRYVIO?"
- are breastfeeding or plan to breastfeed. It is not known if TRYVIO passes into your breastmilk. Do not breastfeed if you take TRYVIO. Talk to your healthcare provider about the best way to feed your baby if you take TRYVIO.

Tell your healthcare provider about all the medicines you take, including prescription and over-the-counter medicines, vitamins, and herbal supplements.

How should I take TRYVIO?

- Take TRYVIO exactly how your healthcare provider tells you to take it and do not stop taking TRYVIO unless your healthcare provider tells you to.
- Swallow TRYVIO tablets whole.
- Take TRYVIO with or without food.
- If you take too much TRYVIO, contact your healthcare provider or Poison Control Center at 1-800-222-1222 or www.poison.org, or go to the nearest hospital emergency room right away.
- If you miss a dose of TRYVIO, skip the missed dose and take the next dose at your regularly scheduled time. Do not take 2 doses in the same day to make up for a missed dose.

What are the possible side effects of TRYVIO?
TRYVIO may cause serious side effects, including:

- Serious birth defects. See "What is the most important information I should know about TRYVIO?"
- Liver problems. TRYVIO may cause liver problems. Your healthcare provider should do blood tests to check your liver before starting treatment and as needed during treatment with TRYVIO. Tell your healthcare provider if you have any of the following symptoms of liver problems during treatment with TRYVIO:

- nausea or vomiting
- pain in the upper right stomach
- tiredness
- loss of appetite

- yellowing of your skin or whites of your eyes
- dark urine
- fever
- itching

- Fluid retention. Fluid retention and swelling are common during treatment with TRYVIO and can be serious. Tell your healthcare provider right away if you have any unusual weight gain, trouble breathing, or swelling of your ankles or legs. Your healthcare provider may treat you with other medicines (diuretics) if you develop fluid retention or swelling.
- Low red blood cell levels (anemia). Anemia is common during treatment with TRYVIO and can be serious. Your healthcare provider will do blood tests to check your red blood cells before starting and as needed during treatment with TRYVIO.
- Decreased sperm count. TRYVIO may cause decreased sperm counts in males and may affect the ability to father a child. Tell your healthcare provider if being able to have children is important to you.

Your healthcare provider may stop treatment with TRYVIO if you develop certain side effects. Tell your healthcare provider if you have any side effect that bothers you or that does not go away.
These are not all the possible side effects of TRYVIO. Call your doctor for medical advice about side effects. You may report side effects to FDA at 1-800-FDA-1088.

How should I store TRYVIO?

- Store TRYVIO tablets at room temperature, between 68°F to 77°F (20°C and 25°C).
- Keep TRYVIO tablets in the original container.
- Tightly close the TRYVIO bottle cap each time after opening.
- The TRYVIO bottle contains a desiccant packet to help keep your tablets dry (protect them from moisture). Do not throw away the desiccant packet and keep it in the bottle.
- Protect TRYVIO from light and moisture.
- Keep TRYVIO and all medicines out of the reach of children.

General information about the safe and effective use of TRYVIO.
Medicines are sometimes prescribed for purposes other than those listed in a Medication Guide. Do not use TRYVIO for a condition for which it was not prescribed. Do not give TRYVIO to other people, even if they have the same symptoms that you have. It may harm them. You can ask your pharmacist or healthcare provider for information about TRYVIO that is written for health professionals.

What are the ingredients in TRYVIO?
Active ingredient: aprocitentan
Inactive ingredients: croscarmellose sodium, hydroxypropyl cellulose, lactose monohydrate, magnesium stearate, and microcrystalline cellulose. Film coating: hydroxypropyl cellulose, iron oxide black, iron oxide red, iron oxide yellow, polyvinyl alcohol, silica colloidal hydrated, talc, titanium dioxide, and triethyl citrate.
Distributed by:
Idorsia Pharmaceuticals US Inc.
One Radnor Corporate Center, Suite 101
100 Matsonford Rd.
Radnor, PA 19087
For more information call 1-833-400-9611 or visit www.TRYVIO.com.

This Medication Guide has been approved by the U.S. Food and Drug Administration.
IDRSTRMG03272025

Issued: X/2025

PRINCIPAL DISPLAY PANEL - 30 Tablet Bottle Carton

NDC 80491-8012-3

TRYVIO™
(aprocitentan)
tablets

12.5 mg

Attention: Dispense the enclosed
Medication Guide to each patient.

Rx only

30 film-coated tablets

idorsia